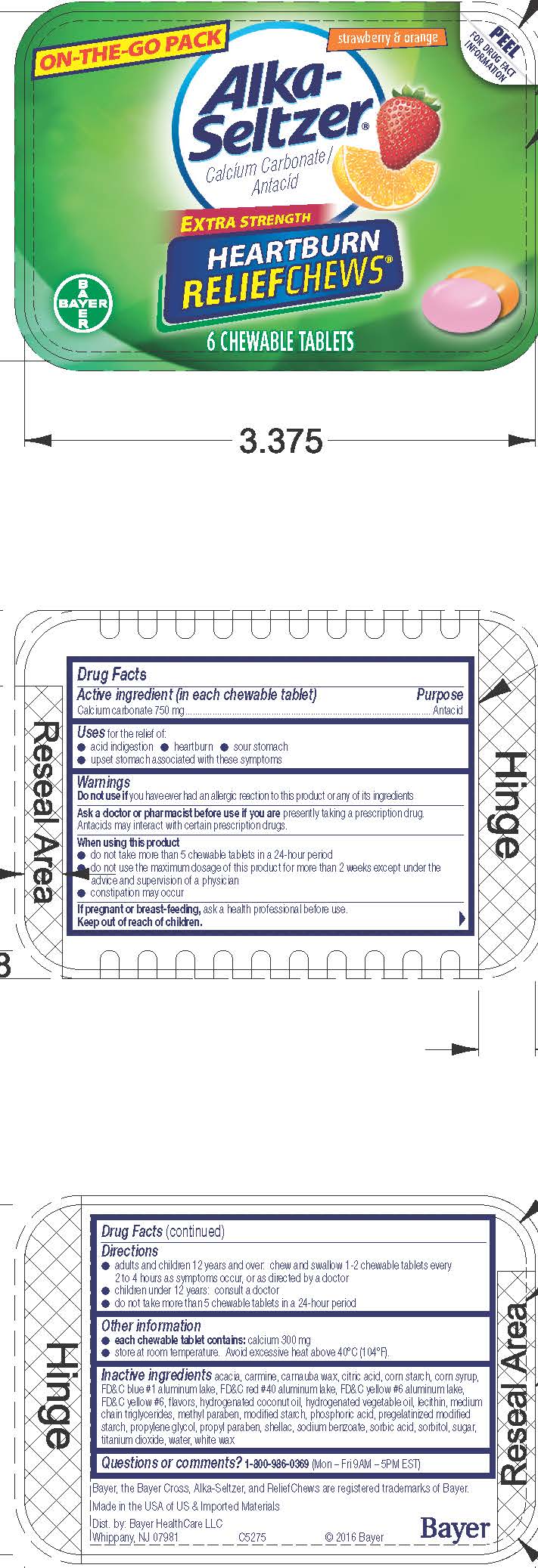 DRUG LABEL: Alka-Seltzer Heartburn ReliefChews Strawberry and Orange
NDC: 0280-0224 | Form: TABLET, CHEWABLE
Manufacturer: Bayer HealthCare LLC.
Category: otc | Type: HUMAN OTC DRUG LABEL
Date: 20251204

ACTIVE INGREDIENTS: CALCIUM CARBONATE 750 mg/1 1
INACTIVE INGREDIENTS: ACACIA; CARNAUBA WAX; CITRIC ACID MONOHYDRATE; STARCH, CORN; CORN SYRUP; FD&C BLUE NO. 1; FD&C RED NO. 40; FD&C YELLOW NO. 6; ALUMINUM OXIDE; HYDROGENATED COCONUT OIL; MEDIUM-CHAIN TRIGLYCERIDES; METHYLPARABEN; PHOSPHORIC ACID; PROPYLENE GLYCOL; WATER; SHELLAC; SODIUM BENZOATE; SORBIC ACID; SORBITOL; SUCROSE; TITANIUM DIOXIDE; WHITE WAX

Alka-Seltzer® Heartburn ReliefChews™ Strawberry & Orange

Drug Facts

Active ingredient (in each chewable tablet)

Calcium carbonate 750 mg

Purpose

Antacid

Uses

for the relief of:

- acid indigestion
- heartburn
- sour stomach
- upset stomach associated with these symptoms

Warnings

Do not use if you have ever had an allergic reaction to this product or any of its ingredients

Ask a doctor or pharmacist before use if you are presently taking a prescription drug. Antacids may interact with certain prescription drugs.

When using this product

- do not take more than 10 chewable tablets in a 24-hour period
- do not use the maximum dosage of this product for more than 2 weeks except under the advice and supervision of a physician
- constipation may occur

PREGNANCY OR BREAST FEEDING

If pregnant or breast-feeding, ask a health professional before use.

Keep out of reach of children.

Directions

- adults and children 12 years and over: chew and swallow 1-2 chewable tablets every 2 to 4 hours as symptoms occur, or as directed by a doctor
- children under 12 years: consult a doctor
- do not take more than 10 chewable tablets in a 24-hour period

Other information

- each chewable tablet contains: calcium 300 mg
- store at room temperature. Avoid excessive heat above 40°C (104°F).

Inactive ingredients

acacia, carmine, carnauba wax, citric acid, corn starch, corn syrup, FD&C blue #1 aluminum lake, FD&C red #40 aluminum lake, FD&C yellow #6 aluminum lake, FD&C yellow #6, flavors, hydrogenated coconut oil, lecithin, medium chain triglycerides, methyl paraben, modified starch, phosphoric acid, pregelatinized modified starch, propylene glycol, propyl paraben, purified water, shellac, sodium benzoate, sorbic acid, sorbitol, sucrose, titanium dioxide, vegetable oil, white wax

Questions or comments?

1-800-986-0369
(Mon – Fri 9AM – 5PM EST) or www.alkaseltzer.com

Dist. by: Bayer HealthCare LLC
Whippany, NJ 07981

PRINCIPAL DISPLAY PANEL - 6 Tablet Blister Pack Carton

ON-THE-GO PACK

PEEL

strawberry & orange

Alka-
Seltzer ®
Calcium Carbonate /Antacid

EXTRA STRENGTH

HEARTBURN
RELIEFCHEWS ™

6 CHEWABLE
TABLETS